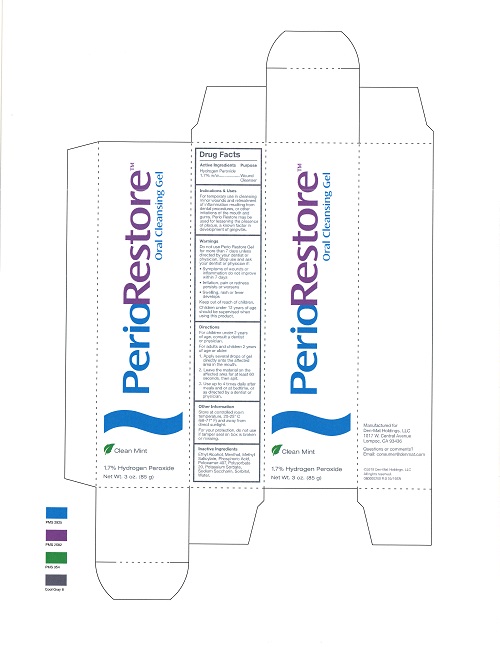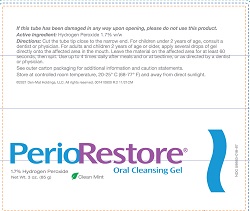 DRUG LABEL: PerioRestore
NDC: 59883-018 | Form: GEL
Manufacturer: DEN-MAT HOLDINGS, LLC.
Category: otc | Type: HUMAN OTC DRUG LABEL
Date: 20231113

ACTIVE INGREDIENTS: HYDROGEN PEROXIDE 17 mg/1 g
INACTIVE INGREDIENTS: SORBITOL; MENTHOL; METHYL SALICYLATE; PHOSPHORIC ACID; POTASSIUM SORBATE; WATER; POLYSORBATE 20; SACCHARIN SODIUM; POLOXAMER 407; ALCOHOL

PerioRestore

Active Ingredients

Hydrogen Peroxide

1.7% w/w

Purpose

Wound Cleanser

Indications & Uses

For temporary use in cleansing minor wounds and retreatment of inflammation resulting from dental procedures, or other irritations of the mouth and gums. Perio Restore may be used for lessening the presence of plaque, a known factor in development of gingivitis.

Warnings

Do not use Perio Restore Gel for more than 7 days unless directed by your dentist or physician. Stop use and ask your dentist or physician if:

- Symptoms of wounds or inflammation do not improve within 7 days.
- Irritation, pain or redness persists or worsens
- Swelling, rash or fever develops

Keep out of reach of children.

Children under 12 years of age should be supervised when using this product.

Directions

For children under 2 years of age, consult dentist or physician.

For adults and children 2 years of age and older:

1. Apply several drops of gel directly onto the affected area in the mouth.

2. Leave the material on the affected area for at least 60 seconds, then spit.

3. Use up to 4 times daily after meals and or a bedtime, or as directed by a dentist or physician.

Other Information

Store at a controlled room temperature, 25-25° C (68-77° F) and away from direct sunlight.

For your protection, do not use if tamper seal on box is broken or missing.

Inactive Ingredients

Ethyl Alcohol, Menthol, Methyl Salicylate, Phosphoric Acid, Poloxamer 407, Polysorbate 20, Potassium Sorbate, Sodium Saccharin, Sorbitol, Water.

Principal Display Panel

PerioRestore™

Oral Cleaning Gel

Clean Mint

1.7% Hydrogen Peroxide

Net Wt. 3 oz. (85 g)

Principal Display Panel

PerioRestor®

Oral Cleansing Gel

1.7% Hydrogen Peroxide

Net Wt. 3 oz. (85 g) Clean Mint

NDC 59883-018-87